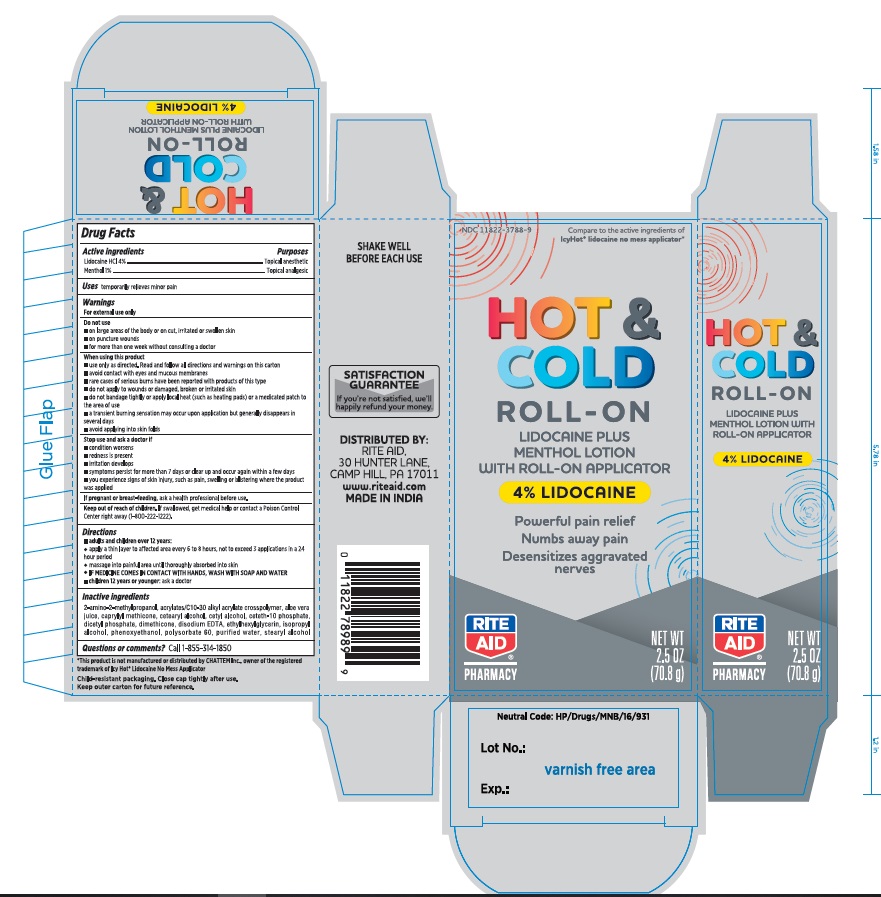 DRUG LABEL: Icy Hot with Lidocaine No-Mess
NDC: 11822-3788 | Form: LIQUID
Manufacturer: Rite Aid Hdgrts Corp
Category: otc | Type: HUMAN OTC DRUG LABEL
Date: 20221120

ACTIVE INGREDIENTS: LIDOCAINE 4 g/100 g; MENTHOL 1 g/100 g
INACTIVE INGREDIENTS: CETYL ALCOHOL; DIMETHICONE; EDETATE DISODIUM; ISOPROPYL ALCOHOL; PHENOXYETHANOL; DIHEXADECYL PHOSPHATE; ETHYLHEXYLGLYCERIN; POLYSORBATE 60; STEARYL ALCOHOL; CETETH-10 PHOSPHATE; CAPRYLYL TRISILOXANE; AMINOMETHYLPROPANOL; CARBOMER INTERPOLYMER TYPE A (ALLYL SUCROSE CROSSLINKED); CETOSTEARYL ALCOHOL; ALOE VERA LEAF; WATER

Icy Hot with Lidocaine No-Mess Applicator

ICY HOT with LIDOCAINE NO MESS

Drug Facts

Active ingredients

Lidocaine HCL

Menthol

Purposes

Lidocaine HCl 4%............................................................................................................................Topical anesthetic

Menthol 1%.......................................................................................................................................Topical analgesic

Use

temporarily relieves minor pain

Warnings

For external use only

Do not use

■ on large areas of the body or on cut, irritated or swollen skin

■ on puncture wounds

■ for more than one week without consulting a doctor

When using this product

■ use only as directed. Read and follow all directions and warnings on this carton.

■ avoid contact with eyes and mucous membranes

■ rare cases of serious burns have been reported with products of this type

■ do not apply to wounds or damaged, broken or irritated skin

■ do not bandage tightly or apply local heat (such as heating pads) or a medicated patch to the area of use

■ a transient burning sensation may occur upon application but generally disappears in several days

■ avoid applying into skin folds

Stop use and ask a doctor if

■ condition worsens

■ redness is present

■ irritation develops

■ symptoms persist for more than 7 days or clear up and occur again within a few days

■ you experience signs of skin injury, such as pain, swelling, or blistering where the product was applied

If pregnant or breast-feeding,

ask a health professional before use.

Keep out of reach of children.

If swallowed, get medical help or contact a Poison Control Center right away.

Directions

adults and children over 12 years:

■ apply a thin layer to affected area not more than 3 to 4 times daily

■ massage into painful area until thoroughly absorbed into skin

■ IF MEDICINE COMES IN CONTACT WITH HANDS, WASH WITH SOAP AND WATER

children 12 years or younger: ask a doctor

Inactive ingredients

2-amino-2methylpropanol, acrylates/C10-30 alkyl acrylate crosspolymer, aloe vera juice, caprylyl methicone, cetearyl alcohol, cetyl alcohol, ceteth-10 phosphate, dicetyl phosphate, dimethicone, disodium EDTA, ethylhexylglycerin, isopropyl alcohol, phenoxyethanol, polysorbate 60, purified water, stearyl alcohol